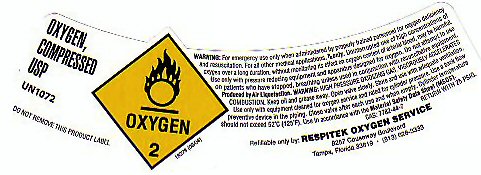 DRUG LABEL: OXYGEN
NDC: 58247-001 | Form: GAS
Manufacturer: Respitek Inc
Category: prescription | Type: HUMAN PRESCRIPTION DRUG LABEL
Date: 20251223

ACTIVE INGREDIENTS: OXYGEN 99 L/100 L

PRODUCT WARNINGS AND PRECAUTIONS

WARNING: HIGH PRESSURE OXIDIZING GAS VIGOROUSLY ACCELERATES COMBUSTION. KEEP OIL AND GREASE AWAY. OPEN VALVE SLOWLY. STORE AND USE WITH ADEQUATE VENTILATION. USE ONLY WITH EQUIPMENT CLEANED FOR OXYGEN SERVICE AND RATED FOR CYLINDER PRESSURE. USE A BACK FLOW PREVENTATIVE DEVICE IN THE PIPING. CLOSE VALVE AFTER EACH USE AND WHEN EMPTY. CYLINDER TEMPERATURE SHOULD NOT EXCEED 52 C (125 F). USE IN ACCORDANCE WITH THE MATERIAL SAFETY DATA SHEET (MSDS) CAS 7782-44-7 RETURN WITH 25 PSIG. PRODUCED BY AIR LIQUEFACTION. REFILLABLE ONLY BY RESPITEK OXYGEN SERVICE.

OXYGEN COMPRESSED LABEL

OXYGEN COMPRESSED USP UN 1072 OXYGEN-2 DO NOT REMOVE THIS PRODUCT LABEL

WARNING: FOR EMERGENCY USE ONLY WHEN ADMINISTERED BY TRAINED PERSONNEL FOR OXYGEN DEFICIENCY AND RESUSCITATION. FOR ALL OTHER MEDICAL APPLICATIONS Rx ONLY. UNINTERRUPTED USE OF HIGH CONCENTRATIONS OF OXYGEN OVER A LONG DURATION WITHOUT MONITORING ITS EFFECT ON OXYGEN CONTENT OF ARTERIAL BLOOD MAY BE HARMFUL. USE ONLY WITH PRESSURE REDUCING EQUIPMENT AND APPARATUS DESIGNED FOR OXYGEN. DO NOT ATTEMPT TO USE ON PATIENTS WHO HAVE STOPPED BREATHING UNLESS USED IN CONJUNCTION WITH RESUSCITATIVE EQUIPMENT.

18278 (08/04)

res